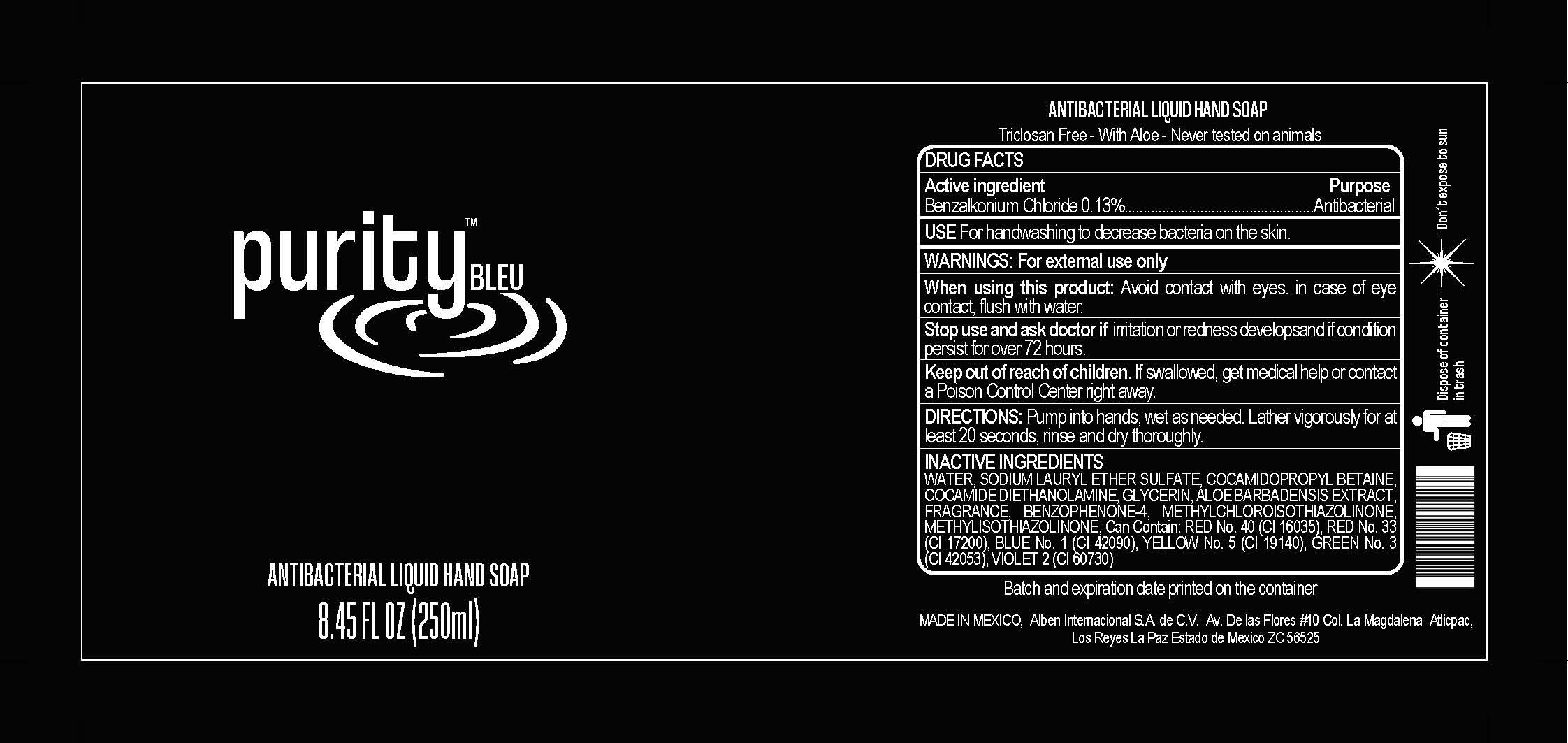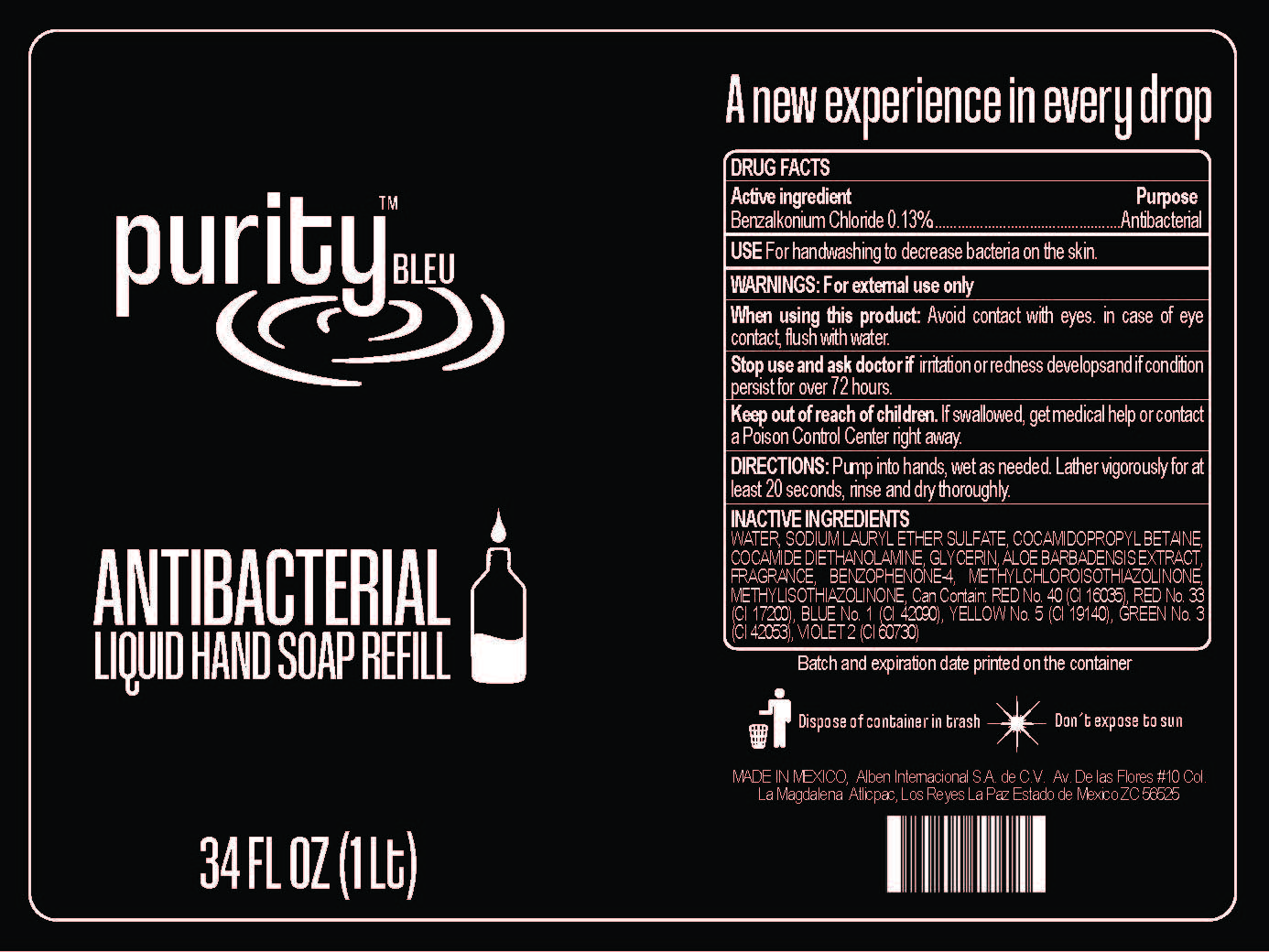 DRUG LABEL: Purity Bleu Antibacterial
NDC: 80955-010 | Form: SOLUTION
Manufacturer: Alben Internacional, S.A. de C.V.
Category: otc | Type: HUMAN OTC DRUG LABEL
Date: 20201028

ACTIVE INGREDIENTS: BENZALKONIUM CHLORIDE 13 g/100 mL
INACTIVE INGREDIENTS: ALOE; BENZOPHENONE-5; METHYLCHLOROISOTHIAZOLINONE; COCO DIETHANOLAMIDE; GLYCERIN; FRAGRANCE CLEAN ORC0600327; SODIUM LAURYL SULFATE; COCAMIDOPROPYL BETAINE; WATER

Active Ingredient(s)

Benzethonium Chloride 0.13% v/v. Purpose: Antibacterial

Purpose

Antibacterial, Hand Soap

Use

Uses - For handwashing to decrease bacteria on the skin

Warnings

For external use only.

Do not use

- in children less than 2 months of age
- on open skin wounds

When using this product keep out of eyes, ears, and mouth. In case of contact with eyes, rinse eyes thoroughly with water.
Stop use and ask a doctor if irritation or rash occurs. These may be signs of a serious condition.
Keep out of reach of children. If swallowed, get medical help or contact a Poison Control Center right away.

Stop use and ask a doctor if irritation or rash occurs. These may be signs of a serious condition.

Keep out of reach of children. If swallowed, get medical help or contact a Poison Control Center right away.

Directions

- Directions - pump into DRY hands - lather vigorously for at least 15 seconds - rinse and dry thoroughly
- Supervise children under 6 years of age when using this product to avoid swallowing.

Other information

- Store between 15-30C (59-86F)
- Avoid freezing and excessive heat above 40C (104F)

Inactive ingredients

WATER, SODIUM LAURYL ETHER SULFATE, COCAMIDOPROPYL BETAINE, COCAMIDE DIETHANOLAMINE, GLYCERIN, ALOE BARBADENSIS EXTRACT, FRAGRANCE, BENZOPHENONE-4, METHYLCHLOROISOTHIAZOLINONE, METHYLISOTHIAZOLINONE, Can Contain: RED No. 40 (CI 16035), RED No. 33 (CI 17200), BLUE No. 1 (CI 42090), YELLOW No. 5 (CI 19140), GREEN No. 3 (CI 42053), VIOLET 2 (CI 60730)

Package Label - Principal Display Panel

250 ml NDC:80955-010-01

1000 ml NDC:80955-010-02